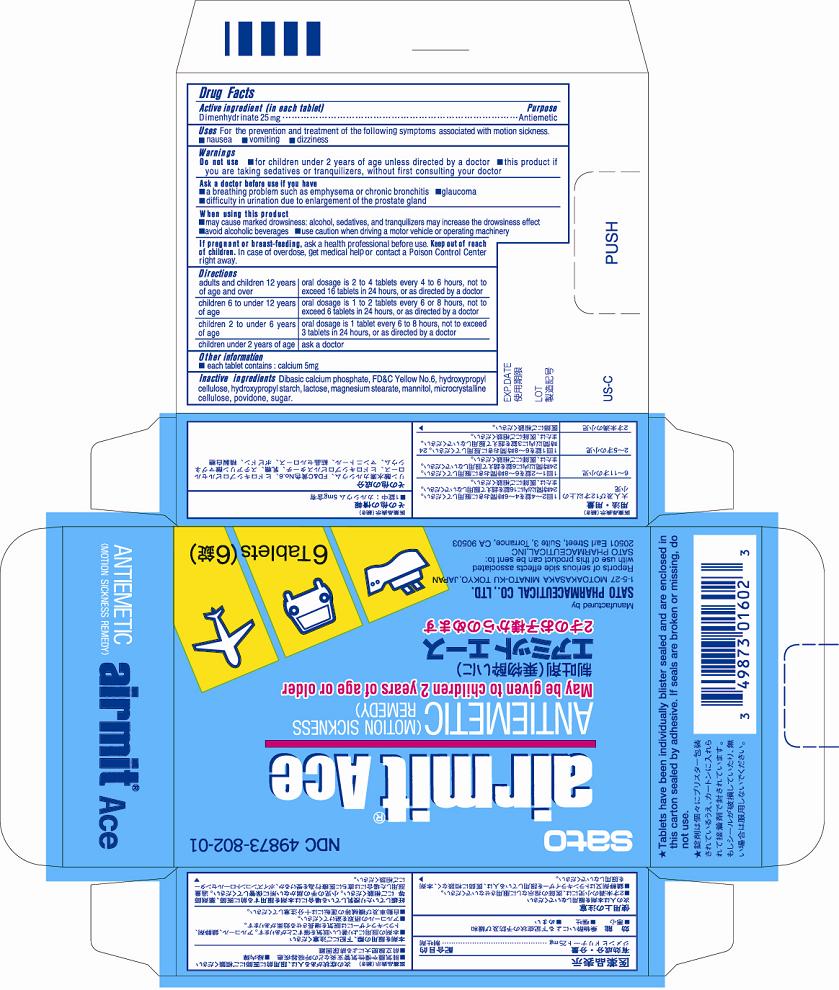 DRUG LABEL: Airmit Ace
NDC: 49873-802 | Form: TABLET
Manufacturer: Sato Pharmaceutical Co., Ltd.
Category: otc | Type: HUMAN OTC DRUG LABEL
Date: 20231201

ACTIVE INGREDIENTS: DIMENHYDRINATE 25 mg/1 1
INACTIVE INGREDIENTS: CALCIUM PHOSPHATE, DIBASIC, ANHYDROUS; FD&C YELLOW NO. 6; HYDROXYPROPYL CORN STARCH (5% SUBSTITUTION BY WEIGHT); HYDROXYPROPYL CELLULOSE; LACTOSE; MAGNESIUM STEARATE; MANNITOL; CELLULOSE, MICROCRYSTALLINE; POVIDONE; SUCROSE

Airmit Ace

Active ingredient (in each tablet)
Dimenhydrinate 25 mg

Purpose
Antiemetic

Uses
For the prevention and treatment of the following symptoms associated with motion sickness
■nausea ■vomiting ■dizziness

Warnings

Do not use

■for children under 2 years of age unless directed by a doctor
■this product if you are taking sedatives or tranquilizers, without first consulting your doctor

Ask a doctor before use if you have
■a breathing problem such as emphysema or chronic bronchitis
■glaucoma
■difficulty in urination due to enlargement of the prostate gland

When using this product
■may cause marked drowsiness: alcohol, sedatives, and tranquilizers may increase the drowsiness effect
■avoid alcoholic beverages
■use caution when driving a motor vehicle or operating machinery

PREGNANCY OR BREAST FEEDING

If pregnant or breast-feeding, ask a health professional before use.

KEEP OUT OF REACH OF CHILDREN

Keep our of reach of children. In case of over dose, get medical help or contact a Poison Control Center right away.

Directions

adults and children 12 years of age and over - oral dosage is 2 to 4 tablets every 4 to 6 hours, not to exceed 16 tablets in 24 hours, or as directed by a doctor
children 6 to under 12 years of age - oral dosage is 1 to 2 tablets every 6 to 8 hours, not to exceed 6 tablets in 24 hours, or as directed by a doctor
children 2 to under 6 years of age - oral dosage is 1 tablet every 6 to 8 hours, not to exceed 3 tablets in 24 hours, or as directed by a doctor
children under 2 years of age - ask a doctor

Other information
■each tablet contains: calcium 5mg

INACTIVE INGREDIENT

Inactive ingredients Dibasic calcium phosphate, FD and C Yellow No. 6, hydroxypropyl cellulose, hydroxypropyl starch, lactose, magnesium stearate, mannitol, microcrystalline cellulose, povidone, sugar.